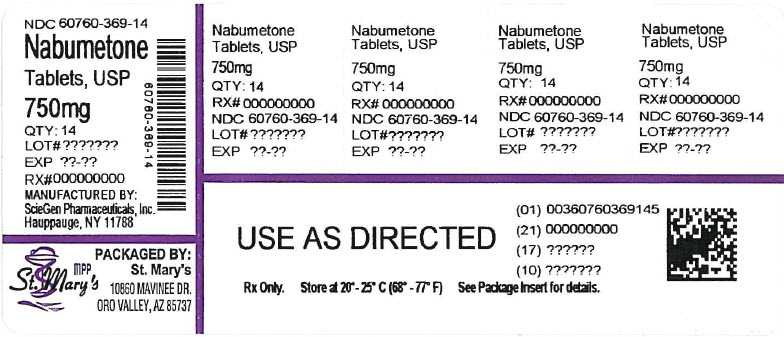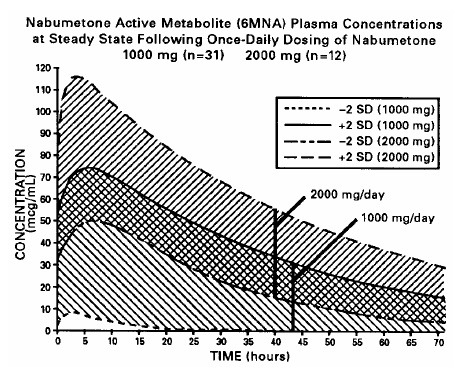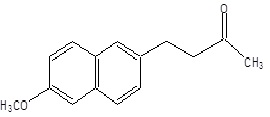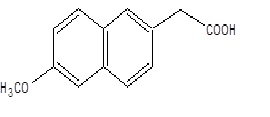 DRUG LABEL: Nabumetone
NDC: 60760-369 | Form: TABLET
Manufacturer: St. Mary's Medical Park Pharmacy
Category: prescription | Type: HUMAN PRESCRIPTION DRUG LABEL
Date: 20260224

ACTIVE INGREDIENTS: NABUMETONE 750 mg/1 1
INACTIVE INGREDIENTS: HYPROMELLOSE, UNSPECIFIED; MICROCRYSTALLINE CELLULOSE; SODIUM LAURYL SULFATE; SODIUM STARCH GLYCOLATE TYPE A POTATO; POLYETHYLENE GLYCOL 400; TITANIUM DIOXIDE

Nabumetone Tablets USP

BOXED WARNING

Cardiovascular Risk

• Nonsteroidal anti-inflammatory drugs (NSAIDs) cause an increased risk of serious cardiovascular thrombotic events, including myocardial infarction and stroke, which can be fatal. This risk may occur early in treatment and may increase with duration of use [see Warnings and Precautions].

• Nabumetone tablets are contraindicated in the setting of coronary artery bypass graft (CABG) surgery [see Contraindications and Warnings].

Gastrointestinal Risk

• NSAIDs cause an increased risk of serious gastrointestinal adverse events including bleeding, ulceration, and perforation of the stomach or intestines, which can be fatal. These events can occur at any time during use and without warning symptoms. Elderly patients are at greater risk for serious gastrointestinal events (see WARNINGS).

DESCRIPTION

Nabumetone is a naphthylalkanone designated chemically as 4-(6-methoxy-2- naphthalenyl)-2-butanone. It has the following structure:

Nabumetone is a white or almost white crystalline substance with a molecular weight of 228.3. It is nonacidic, freely soluble in acetone, sparingly soluble in alcohol and in methanol, practically insoluble in water. It has an n-octanol:phosphate buffer partition coefficient of 2400 at pH 7.4.

Tablets for Oral Administration: Each white coloured, oval shaped, biconvex, film coated tablet contains 500 mg or 750 mg of nabumetone. Inactive ingredients consists of hypromellose, microcrystalline cellulose, sodium lauryl sulfate, sodium starch glycolate and opadry white OY 58900 [hypromellose, polyethylene glycol 400, and titanium dioxide].

CLINICAL PHARMACOLOGY

Nabumetone is a non-steroidal anti-inflammatory drug (NSAID) that exhibits anti-inflammatory, analgesic, and antipyretic properties in pharmacologic studies. As with other non-steroidal anti-inflammatory agents, its mode of action is not known; however, the ability to inhibit prostaglandin synthesis may be involved in the anti-inflammatory effect.

The parent compound is a prodrug, which undergoes hepatic biotransformation to the active component, 6-methoxy-2-naphthylacetic acid (6MNA), that is a potent inhibitor of prostaglandinsynthesis.

It is acidic and has an n-octanol:phosphate buffer partition coefficient of 0.5 at pH 7.4.

Pharmacokinetics: After oral administration, approximately 80% of a radiolabelled dose of nabumetone is found in the urine, indicating that nabumetone is well absorbed from the gastrointestinal tract. Nabumetone itself is not detected in the plasma because, after absorption, it undergoes rapid biotransformation to the principal active metabolite, 6-methoxy-2-naphthylacetic acid (6MNA). Approximately 35% of a 1,000 mg oral dose of nabumetone is converted to 6MNA and 50% is converted into unidentified metabolites which are subsequently excreted in the urine. Following oral administration of nabumetone, 6MNA exhibits pharmacokinetic characteristics that generally follow a one-compartment model with first order input and first order elimination.

6MNA is more than 99% bound to plasma proteins. The free fraction is dependent on total concentration of 6MNA and is proportional to dose over the range of 1,000 mg to 2,000 mg. It is 0.2% to 0.3% at concentrations typically achieved following administration of 1,000 mg of nabumetone and is approximately 0.6% to 0.8% of the total concentrations at steady state following daily administration of 2,000 mg.

Steady-state plasma concentrations of 6MNA are slightly lower than predicted from single-dose data. This may result from the higher fraction of unbound 6MNA which undergoes greater hepatic clearance.

Coadministration of food increases the rate of absorption and subsequent appearance of 6MNA in the plasma but does not affect the extent of conversion of nabumetone into 6MNA. Peak plasma concentrations of 6MNA are increased by approximately one third.

Coadministration with an aluminum-containing antacid had no significant effect on the bioavailability of 6MNA.

Table 1. Mean Pharmacokinetic Parameters of Nabumetone Active Metabolite (6MNA) at Steady State Following Oral Administration of 1,000 mg or 2,000 mg Doses of Nabumetone

Abbreviation (units) | Young Adults Mean ± SD 1,000 mgn = 31 | Young Adults Mean ± SD 2,000 mgn = 12 | Elderly Mean ± SD 1,000 mgn = 27
Tmax(hr) | 3.0 (1.0 to 12.0) | 2.5 (1.0 to 8.0) | 4.0 (1.0 to 10.0)
t½(hr) | 22.5 ± 3.7 | 26.2 ± 3.7 | 29.8 ± 8.1
CLss/F (mL/min) | 26.1 ± 17.3 | 21.0 ± 4.0 | 18.6 ± 13.4
Vdss/F (L) | 55.4 ± 26.4 | 53.4 ± 11.3 | 50.2 ± 25.3

The simulated curves in the graph below illustrate the range of active metabolite plasma concentrations that would be expected from 95% of patients following 1,000 mg to 2,000 mg doses to steady state. The cross-hatched area represents the expected overlap in plasma concentrations due to intersubject variation following oral administration of 1,000 mg to 2,000 mg of nabumetone.

6MNA undergoes biotransformation in the liver, producing inactive metabolites that are eliminated as both free metabolites and conjugates. None of the known metabolites of 6MNA has been detected in plasma. Preliminary in vivo and in vitro studies suggest that unlike other NSAIDs, there is no evidence of enterohepatic recirculation of the active metabolite. Approximately 75% of a radiolabelled dose was recovered in urine in 48 hours. Approximately 80% was recovered in 168 hours. A further 9% appeared in the feces. In the first 48 hours, metabolites consisted of:

–nabumetone, unchanged | not detectable
–6-methoxy-2-naphthylacetic acid | <1%
(6MNA), unchanged
–6MNA, conjugated | 11%
–6-hydroxy-2-naphthylacetic acid | 5%
(6HNA), unchanged
–6HNA, conjugated | 7%
–4-(6-hydroxy-2-naphthyl)-butan-2-ol, | 9%
Conjugated
–O-desmethyl-nabumetone, conjugated | 7%
–unidentified minor metabolites | 34%
Total % Dose: | 73%

Following oral administration of dosages of 1,000 mg to 2,000 mg to steady state, the mean plasma clearance of 6MNA is 20 to 30 mL/min and the elimination half-life is approximately 24 hours.

Elderly Patients: Steady-state plasma concentrations in elderly patients were generally higher than in young healthy subjects (see Table 1 for summary of pharmacokinetic parameters).

Renal Insufficiency: In moderate renal insufficiency patients (creatinine clearance 30 to 49 mL/min), the terminal half-life of 6MNA was increased by approximately 50% (39.2 ± 7.8 hrs, N=12) compared to the normal subjects (26.9 ± 3.3 hrs, N=13), and there was a 50% increase in the plasma levels of unbound 6MNA.

Additionally, the renal excretion of 6MNA in the moderate renal impaired patients decreased on average by 33% compared to that in the normal patients. A similar increase in the mean terminal half-life of 6MNA was seen in a small study of patients with severe renal dysfunction (creatine clearance < 30 mL/min). In patients undergoing hemodialysis, steady-state plasma concentrations of the active metabolite 6MNA were similar to those observed in healthy subjects. Due to extensive protein binding, 6MNA is not dialyzable.

Dosage adjustment of nabumetone generally is not necessary in patients with mild renal insufficiency (³ 50 mL/min). Caution should be used in prescribing nabumetone to patients with moderate or severe renal insufficiency. The maximum starting doses of nabumetone in patients with moderate or severe renal insufficiency should not exceed 750 mg or 500 mg, respectively once daily. Following careful monitoring of renal function in patients with moderate or severe renal insufficiency, daily doses may be increased to a maximum of 1,500 mg and 1,000 mg, respectively (see WARNINGS, Renal Effects).

Hepatic Impairment: Data in patients with severe hepatic impairment are limited. Biotransformation of nabumetone to 6MNA and the further metabolism of 6MNA to inactive metabolites is dependent on hepatic function and could be reduced in patients with severe hepaticimpairment (history of or biopsy-proven cirrhosis).

Special Studies: Gastrointestinal: Nabumetone was compared to aspirin in inducing gastrointestinal blood loss. Food intake was not monitored. Studies utilizing^51Cr-tagged red blood cells in healthy males showed no difference in fecal blood loss after 3 or 4 weeks’ administration of 1,000 mg or 2,000 mg of nabumetone daily when compared to either placebo-treated or nontreated subjects. In contrast, aspirin 3,600 mg daily produced an increase in fecal blood loss when compared to subjects who received nabumetone, placebo, or no treatment. The clinical relevance of the data is unknown.

The following endoscopy trials entered patients who had been previously treated with NSAIDs. These patients had varying baseline scores and different courses of treatment. The trials were not designed to correlate symptoms and endoscopy scores. The clinical relevance of these endoscopy trials, i.e., either G.I. symptoms or serious G.I. events, is not known.

Ten endoscopy studies were conducted in 488 patients who had baseline and post-treatment endoscopy. In 5 clinical trials that compared a total of 194 patients on 1,000 mg of nabumetone daily or naproxen 250 mg or 500 mg twice daily for 3 to 12 weeks, treatment with nabumetone resulted in fewer patients with endoscopically detected lesions (>3 mm). In 2 trials a total of 101 patients administered 1,000 mg or 2,000 mg of nabumetone daily or piroxicam 10 mg to 20 mg for 7 to 10 days, there were fewer patients treated with nabumetone with endoscopically detected lesions. In 3 trials of a total of 47 patients on 1,000 mg of nabumetone daily or indomethacin 100 mg to 150 mg daily for 3 to 4 weeks, the endoscopy scores were higher with indomethacin. Another 12-week trial in a total of 171 patients compared the results of treatment with 1,000 mg of nabumetone daily to ibuprofen 2,400 mg/day and ibuprofen 2,400 mg/day plus misoprostol 800 mcg/day. The results showed that patients treated with nabumetone had a lower number of endoscopically detected lesions (>5 mm) than patients treated with ibuprofen alone but comparable to the combination of ibuprofen plus misoprostol. The results did not correlate with abdominal pain.

Other: In 1-week, repeat-dose studies in healthy volunteers, 1,000 mg of nabumetone daily had little effect on collagen-induced platelet aggregation and no effect on bleeding time. In comparison, naproxen 500 mg daily suppressed collagen-induced platelet aggregation and significantly increased bleeding time.

CLINICAL TRIALS

Osteoarthritis: The use of nabumetone in relieving the signs and symptoms of osteoarthritis (OA) was assessed in double-blind, controlled trials in which 1,047 patients were treated for 6 weeks to 6 months. In these trials, nabumetone in a dose of 1,000 mg/day administered at night was comparable to naproxen 500 mg/day and to aspirin 3,600 mg/day.

Rheumatoid Arthritis: The use of nabumetone in relieving the signs and symptoms of rheumatoid arthritis (RA) was assessed in double-blind, randomized, controlled trials in which 770 patients were treated for 3 weeks to 6 months. nabumetone, in a dose of 1,000 mg/day administered at night, was comparable to naproxen 500 mg/day and to aspirin 3,600 mg/day.

In controlled clinical trials of rheumatoid arthritis patients, nabumetone has been used in combination with gold, d-penicillamine, and corticosteroids.

Patient Exposure in Clinical Trials of Osteoarthritis and Rheumatoid Arthritis:In clinical trials with osteoarthritis and rheumatoid arthritis patients, most patients responded to nabumetone in doses of 1,000 mg/day administered nightly; total daily dosages up to 2,000 mg were used. In open-labelled studies, 1,490 patients were permitted dosage increases and were followed for approximately 1 year (mode). Twenty percent of patients (n = 294) were withdrawn for lack of effectiveness during the first year of these open-labelled studies. The following table provides patient-exposure to doses used in the US clinical trials:

Table 2. Clinical Double-Blinded and Open-Labelled Trials of Nabumetone in Osteoarthritis and Rheumatoid Arthritis

Mean/Mode Duration Dose of Number of Patientsof Treatment (yr) Nabumetone OA RA OA RA
500 mg | 17 | 6 | 0.4/- | 0.2/-
1,000 mg | 917 | 701 | 1.2/1 | 1.4/1
1,500 mg | 645 | 224 | 2.3/1 | 1.7/1
2,000 mg | 15 | 100 | 0.6/1 | 1.3/1

As with other NSAIDs, the lowest dose should be sought for each patient. Patients weighing under 50 kg may be less likely to require dosages beyond 1,000 mg; therefore, after observing the response to initial therapy, the dose should be adjusted to meet individual patients’ requirements.

INDICATIONS AND USAGE

Carefully consider the potential benefits and risks of nabumetone tablets and other treatment options before deciding to use nabumetone tablets. Use the lowest effective dose for the shortest duration consistent with individual patient treatment goals (see WARNINGS).

Nabumetone tablets are indicated for relief of signs and symptoms of osteoarthritis and rheumatoid arthritis.

CONTRAINDICATIONS

Nabumetone tablets are contraindicated in patients with known hypersensitivity to nabumetone or its excipients.

Nabumetone tablets should not be given to patients who have experienced asthma, urticaria, or allergic-type reactions after taking aspirin or other NSAIDs. Severe, rarely fatal, anaphylactic-like reactions to NSAIDs have been reported in such patients (see WARNINGS, Anaphylactoid Reactions, and PRECAUTIONS, General, Preexisting Asthma).

In the setting of coronary artery bypass graft (CABG) surgery [see Warnings].

WARNINGS

Cardiovascular Effects

Cardiovascular Thrombotic Events: Clinical trials of several COX-2 selective and nonselective NSAIDs of up to three years duration have shown an increased risk of serious cardiovascular (CV) thrombotic events, including myocardial infarction (MI) and stroke, which can be fatal. Based on available data, it is unclear that the risk for CV thrombotic events is similar for all NSAIDs. The relative increase in serious CV thrombotic events over baseline conferred by NSAID use appears to be similar in those with and without known CV disease or risk factors for CV disease. However, patients with known CV disease or risk factors had a higher absolute incidence of excess serious CV thrombotic events, due to their increased baseline rate. Some observational studies found that this increased risk of serious CV thrombotic events began as early as the first weeks of treatment. The increase in CV thrombotic risk has been observed most consistently at higher doses.

To minimize the potential risk for an adverse CV event in NSAID-treated patients, use the lowesteffective dose for the shortest duration possible. Physicians and patients should remain alert for the development of such events, throughout the entire treatment course, even in the absence of previous CV symptoms. Patients should be informed about the symptoms of serious CV events and the steps to take if they occur.

There is no consistent evidence that concurrent use of aspirin mitigates the increased risk of serious CV thrombotic events associated with NSAID use. The concurrent use of aspirin and an NSAID, such as nabumetone, increases the risk of serious gastrointestinal (GI) events [see Warnings].

Status Post Coronary Artery Bypass Graft (CABG) SurgeryTwo large, controlled clinical trials of a COX-2 selective NSAID for the treatment of pain in the first 10–14 days following CABG surgery found an increased incidence of myocardial infarctionand stroke. NSAIDs are contraindicated in the setting of CABG [see Contraindications].

Post-MI Patients

Observational studies conducted in the Danish National Registry have demonstrated that patients treated with NSAIDs in the post-MI period were at increased risk of reinfarction, CV-related death, and all-cause mortality beginning in the first week of treatment. In this same cohort, the incidence of death in the first year post MI was 20 per 100 person years in NSAID-treated patients compared to 12 per 100 person years in non-NSAID exposed patients. Although the absolute rate of death declined somewhat after the first year post-MI, the increased relative risk of death in NSAID users persisted over at least the next four years of f

ollow-up.

Avoid the use of nabumetone tablets in patients with a recent MI unless the benefits are expected to outweigh the risk of recurrent CV thrombotic events. If nabumetone tablets are used in patients with a recent MI, monitor patients for signs of cardiac ischemia.

Hypertension: NSAIDs, including nabumetone, can lead to onset of new hypertension or worsening of preexisting hypertension, either of which may contribute to the increased incidence of CV events. Patients taking thiazides or loop diuretics may have impaired response to these therapies when taking NSAIDs. NSAIDs, including nabumetone, should be used with caution in patients with hypertension. Blood pressure (BP) should be monitored closely during the initiation of NSAID treatment and throughout the course of therapy.

Heart Failure and EdemaThe Coxib and traditional NSAID Trialists’ Collaboration meta-analysis of randomized controlled trials demonstrated an approximately two-fold increase in hospitalizations for heart failure in COX-2 selective-treated patients and nonselective NSAID-treated patients compared toplacebo-treated patients. In a Danish National Registry study of patients with heart failure, NSAID use increased the risk of MI, hospitalization for heart failure, and death. Additionally, fluid retention and edema have been observed in some patients treated with NSAIDs. Use of nabumetone may blunt the CV effects of several therapeutic agents used to treat these medical conditions [e.g., diuretics, ACE inhibitors, or angiotensin receptor blockers (ARBs)] [see Drug Interactions ].

Avoid the use of nabumetone tablets in patients with severe heart failure unless the benefits are expected to outweigh the risk of worsening heart failure. If nabumetone tablets are used in patients with severe heart failure, monitor patients for signs of worsening heart failure.

Gastrointestinal Effects― Risk of Ulceration, Bleeding, and Perforation: NSAIDs, including nabumetone, can cause serious gastrointestinal (GI) adverse events including inflammation, bleeding, ulceration, and perforation of the stomach, small intestine, or large intestine, which can be fatal. These serious adverse events can occur at any time, with or without warning symptoms, in patients treated with NSAIDs. Only 1 in 5 patients, who develop a serious upper GI adverse event on NSAID therapy, is symptomatic. Upper GI ulcers, gross bleeding, or perforation caused by NSAIDs occur in approximately 1% of patients treated for 3 to 6 months, and in about 2 to 4% of patients treated for 1 year. These trends continue with longer duration of use, increasing the likelihood of developing a serious GI event at some time during the course of therapy. However, even short-term therapy is not without risk.

In controlled clinical trials involving 1,677 patients treated with nabumetone (1,140 followed for 1 year and 927 for 2 years), the cumulative incidence of peptic ulcers was 0.3% (95% CI; 0%, 0.6%) at 3 to 6 months, 0.5% (95% CI; 0.1%, 0.9%) at 1 year and 0.8% (95% CI; 0.3%, 1.3%) at 2 years. In patients with active peptic ulcer, physicians must weigh the benefits of therapy with nabumetone against possible hazards, institute an appropriate ulcer treatment regimen and monitor the patients’ progress carefully.

NSAIDs should be prescribed with extreme caution in those with a prior history of ulcer disease or gastrointestinal bleeding. Patients with a prior history of peptic ulcer disease and/or gastrointestinal bleeding who use NSAIDs have a greater than 10-fold increased risk for developing a GI bleed compared to patients with neither of these risk factors. Other factors that increase the risk for GI bleeding in patients treated with NSAIDs include concomitant use of oral corticosteroids or anticoagulants, longer duration of NSAID therapy, smoking, use of alcohol, older age, and poor general health status. Most spontaneous reports of fatal GI events are in elderly or debilitated patients and therefore, special care should be taken in treating this population.

To minimize the potential risk for an adverse GI event in patients treated with an NSAID, the lowest effective dose should be used for the shortest possible duration. Patients and physicians should remain alert for signs and symptoms of GI ulceration and bleeding during NSAID therapy and promptly initiate additional evaluation and treatment if a serious GI adverse event is suspected. This should include discontinuation of the NSAID until a serious GI adverse event is ruled out. For high risk patients, alternate therapies that do not involve NSAIDs should be considered.

Renal Effects: Long-term administration of NSAIDs has resulted in renal papillary necrosis and other renal injury. Renal toxicity has also been seen in patients in whom renal prostaglandins have a compensatory role in the maintenance of renal perfusion. In these patients, administration of an NSAID results in a dose-dependent decrease in prostaglandin synthesis and, secondarily, in a reduction of renal blood flow, which may precipitate overt renal decompensation. Patients at greatest risk of this reaction are those with impaired renal function, heart failure, liver dysfunction, those taking diuretics, and the elderly. Discontinuation of NSAID therapy is typically followed by recovery to the pretreatment state.

Advanced Renal Disease: No information is available from controlled clinical studies regarding the use of nabumetone in patients with advanced renal disease. Therefore, treatment with nabumetone is not recommended in these patients with advanced renal disease. If nabumetone therapy must be initiated, close monitoring of the patient’s renal function is advisable.

Because nabumetone undergoes extensive hepatic metabolism, no adjustment of the dosage of nabumetone is generally necessary in patients with mild renal insufficiency; however, as with all NSAIDs, patients with impaired renal function should be monitored more closely than patients with normal renal function (see CLINICAL PHARMACOLOGY, Pharmacokinetics, Renal Insufficiency). In subjects with moderate renal impairment (creatinine clearance 30 to 49 mL/min) there is a 50% increase in unbound plasma 6MNA and dose adjustment may be warranted. The oxidized and conjugated metabolites of 6MNA are eliminated primarily by the kidneys.

Anaphylactoid Reactions: As with other NSAIDs, anaphylactoid reactions may occur in patients without known prior exposure to nabumetone. Nabumetone should not be given to patients with the aspirin triad. This symptom complex typically occurs in asthmatic patients who experience rhinitis with or without nasal polyps, or who exhibit severe, potentially fatal bronchospasm after taking aspirin or other NSAIDs (see CONTRAINDICATIONS and PRECAUTIONS, General, Preexisting Asthma). Emergency help should be sought in cases where an anaphylactoid reaction occurs.

Skin Reactions: NSAIDs, including nabumetone, can cause serious skin adverse events such as exfoliative dermatitis, Stevens-Johnson Syndrome (SJS), and toxic epidermal necrolysis (TEN), which can be fatal. These serious events may occur without warning. Patients should be informed about the signs and symptoms of serious skin manifestations and use of the drug should be discontinued at the first appearance of skin rash or any other sign of hypersensitivity.

Pregnancy: In late pregnancy, as with other NSAIDs, nabumetone should be avoided because it may cause premature closure of the ductus arteriosus.

PRECAUTIONS

General

Nabumetone cannot be expected to substitute for corticosteroids or to treat corticosteroid insufficiency. Abrupt discontinuation of corticosteroids may lead to disease exacerbation. Patients on prolonged corticosteroid therapy should have their therapy tapered slowly if a decision is made to discontinue corticosteroids.

The pharmacological activity of nabumetone in reducing fever and inflammation may diminish the utility of these diagnostic signs in detecting complications of presumed noninfectious, painful conditions.

Hepatic Effects: Borderline elevations of 1 or more liver function tests may occur in up to 15% of patients taking NSAIDs including nabumetone. These laboratory abnormalities may progress, may remain unchanged, or may be transient with continuing therapy. Notable elevations of ALT or AST (approximately 3 or more times the upper limit of normal) have been reported in approximately 1% of patients in clinical trials with NSAIDs. In addition, rare cases of severe hepatic reactions, including jaundice and fatal fulminant hepatitis, liver necrosis and hepatic failure, some of them with fatal outcomes have been reported. A patient with symptoms and/or signs suggesting liver dysfunction, or in whom an abnormal liver test has occurred, should be evaluated for evidence of the development of a more severe hepatic reaction while on therapy with nabumetone. If clinical signs and symptoms consistent with liver disease develop, or if systemic manifestations occur (e.g., eosinophilia, rash, etc.), nabumetone should be discontinued.

Hematological Effects: Anemia is sometimes seen in patients receiving NSAIDS, including nabumetone. This may be due to fluid retention, occult or gross GI blood loss, or an incompletely described effect upon erythropoiesis. Patients on long-term treatment with NSAIDs, including nabumetone, should have their hemoglobin or hematocrit checked if they exhibit any signs or symptoms of anemia.

NSAIDs inhibit platelet aggregation and have been shown to prolong bleeding time in some patients. Unlike aspirin, their effect on platelet function is quantitatively less, of shorter duration, and reversible. Patients receiving nabumetone who may be adversely affected by alterations in platelet function, such as those with coagulation disorders or patients receiving anticoagulants, should be carefully monitored (see CLINICAL PHARMACOLOGY, Special Studies, Other).

Preexisting Asthma: Patients with asthma may have aspirin-sensitive asthma. The use of aspirin in patients with aspirin-sensitive asthma has been associated with severe bronchospasm which can be fatal. Since cross reactivity, including bronchospasm, between aspirin and other non-steroidal anti-inflammatory drugs has been reported in such aspirin-sensitive patients, nabumetone should not be administered to patients with this form of aspirin sensitivity and should be used with caution in patients with preexisting asthma.

Photosensitivity: Based on ultraviolet (U.V.) light photosensitivity testing, nabumetone may be associated with more reactions to sun exposure than might be expected based on skin tanning types.

Information for Patients:

Patients should be informed of the following information before initiating therapy with an NSAID and periodically during the course of ongoing therapy. Patients should also be encouraged to read the NSAID Medication Guide that accompanies each prescription dispensed.

1. Cardiovascular Thrombotic Events: Advise patients to be alert for the symptoms of cardiovascular thrombotic events, including chest pain, shortness of breath, weakness, or slurring of speech, and to report any of these symptoms to their health care provider immediately [see Warnings].

2. Nabumetone, like other NSAIDs, can cause GI discomfort and, rarely, serious GI side effects, such as ulcers and bleeding, which may result in hospitalization and even death. Although serious GI tract ulcerations and bleeding can occur without warning symptoms, patients should be alert for the signs and symptoms of ulcerations and bleeding, and should ask for medical advice when observing any indicative sign or symptoms including epigastric pain, dyspepsia, melena, and hematemesis. Patients should be apprised of the importance of this follow-up (see WARNINGS, Gastrointestinal Effects―Risk of Ulceration, Bleeding, and Perforation).

3. Nabumetone, like other NSAIDs, can cause serious skin side effects such as exfoliative dermatitis, SJS, and TEN, which may result in hospitalizations and even death. Although serious skin reactions may occur without warning, patients should be alert for the signs and symptoms of skin rash and blisters, fever, or other signs of hypersensitivity such as itching, and should ask for medical advice when observing any indicative signs or symptoms. Patients should be advised to stop the drug immediately if they develop any type of rash and contact their physicians as soon as possible

4. Heart Failure and Edema: Advise patients to be alert for the symptoms of congestive heart failure including shortness of breath, unexplained weight gain, or edema and to contact their healthcare provider if such symptoms occur [see Warnings].

5. Patients should be informed of the warning signs and symptoms of hepatotoxicity (e.g., nausea, fatigue, lethargy, pruritus, jaundice, right upper quadrant tenderness, and “flu-like” symptoms). If these occur, patients should be instructed to stop therapy and seek immediate medical therapy.

6. Patients should be informed of the signs of an anaphylactoid reaction (e.g. difficulty breathing, swelling of the face or throat). If these occur, patients should be instructed to seek immediate emergency help (see WARNINGS).

7. In late pregnancy, as with other NSAIDs, nabumetone should be avoided because it may cause premature closure of the ductus arteriosus.

Laboratory Tests

Because serious G.I. tract ulceration and bleeding can occur without warning symptoms, physicians should monitor for signs and symptoms of GI bleeding. Patients on long-term treatment with NSAIDs, should have their CBC and a chemistry profile checked periodically. If clinical signs and symptoms consistent with liver or renal disease develop, systemic manifestations occur (e.g., eosinophilia, rash, etc.) or if abnormal liver tests persist or worsen, nabumetone should be discontinued.

Drug Interactions

ACE-inhibitors: Reports suggest that NSAIDs may diminish the antihypertensive effect of ACE-inhibitors. This interaction should be given consideration in patients taking NSAIDs concomitantly with ACE-inhibitors.

Aspirin: When nabumetone is administered with aspirin, its protein binding is reduced, although the clearance of free nabumetone is not altered. The clinical significance of this interaction is not known; however, as with other NSAIDs, concomitant administration of nabumetone and aspirin is not generally recommended because of the potential of increased adverse effects.

Diuretics: Clinical studies, as well as post marketing observations, have shown that nabumetone can reduce the natriuretic effect of furosemide and thiazides in some patients. This response has been attributed to inhibition of renal prostaglandin synthesis. During concomitant therapy with NSAIDs, the patient should be observed closely for signs of renal failure (see PRECAUTIONS, Renal Effects), as well as to assure diuretic efficacy.

Lithium : NSAIDs have produced an elevation of plasma lithium levels and a reduction in renal lithium clearance. The mean minimum lithium concentration increased 15% and the renal clearance was decreased by approximately 20%. These effects have been attributed to inhibition of renal prostaglandin synthesis by the NSAID. Thus, when NSAIDs and lithium are administered concurrently, subjects should be observed carefully for signs of lithium toxicity.

Methotrexate: NSAIDs have been reported to competitively inhibit methotrexate accumulation in rabbit kidney slices. This may indicate that they could enhance the toxicity of methotrexate. Caution should be used when NSAIDs are administered concomitantly with methotrexate.

Warfarin: The effects of warfarin and NSAIDs on GI bleeding are synergistic, such that users of both drugs together have a risk of serious GI bleeding higher than users of either drug alone.

In vitro studies have shown that, because of its affinity for protein, 6MNA may displace other protein-bound drugs from their binding site. Caution should be exercised when administering nabumetone with warfarin since interactions have been seen with other NSAIDs.

Concomitant administration of an aluminum-containing antacid had no significant effect on the bioavailability of 6MNA. When administered with food or milk, there is more rapid absorption; however, the total amount of 6MNA in the plasma is unchanged (see CLINICAL PHARMACOLOGY, Pharmacokinetics).

Carcinogenesis, Mutagenesis, Impairment of Fertility

In 2-year studies conducted in mice and rats, nabumetone had no statistically significant tumorigenic effect. Nabumetone did not show mutagenic potential in the Ames test and mouse micronucleus test in vivo; however, nabumetone- and 6MNA-treated lymphocytes in culture showed chromosomal aberrations at 80 mcg/mL and higher concentrations (equal to the average human exposure to nabumetone at the maximum recommended dose).

Impairment of Fertility: Nabumetone did not impair fertility of male or female rats treated orally at doses of 320 mg/kg/day (1,888 mg/m^2) before mating.

Pregnancy: Teratogenic Effects: Pregnancy: Category C.

Reproductive studies conducted in rats and rabbits have not demonstrated evidence of developmental abnormalities. However, animal reproduction studies are not always predictive of human response. There are no adequate, well-controlled studies in pregnant women. Nabumetone should be used in pregnancy only if the potential benefit justifies the potential risk to the fetus.

Nonteratogenic Effects: Because of the known effects of non-steroidal anti-inflammatory drugs on the fetal cardiovascular system (closure of ductus arteriosus), use during pregnancy (particularly late pregnancy) should be avoided.

Labor and Delivery: In rat studies with NSAIDs, as with other drugs known to inhibit prostaglandin synthesis, an increased incidence of dystocia, delayed parturition, and decreased pup survival occurred.

The effects of nabumetone on labor and delivery in pregnant women are unknown.

Nursing Mothers

It is not known whether this drug is excreted in human milk, however 6MNA is excreted in the milk of lactating rats. Because many drugs are excreted in human milk and because of the potential for serious adverse reactions in nursing infants from nabumetone, a decision should be made whether to discontinue nursing or to discontinue the drug, taking into account the importance of the drug to the mother.

Pediatric Use

Safety and effectiveness in pediatric patients have not been established.

Geriatric Use

As with any NSAIDs, caution should be exercised in treating the elderly (65 years and older). Of the 1,677 patients in US clinical studies who were treated with nabumetone, 411 patients (24%) were 65 years or older; 22 patients (1%) were 75 years or older. No overall differences in efficacy or safety were observed between these older patients and younger ones. Similar results were observed in a 1-year, non-US postmarketing surveillance study of 10,800 patients treated with nabumetone, of whom 4,577 patients (42%) were 65 years or older.

ADVERSE REACTIONS

Adverse reaction information was derived from blinded-controlled and open-labelled clinical trials and from worldwide marketing experience. In the description below, rates of the more common events (greater than 1%) and many of the less common events (less than 1%) represent results of US clinical studies.

Of the 1,677 patients who received nabumetone during US clinical trials, 1,524 were treated for at least 1 month, 1,327 for at least 3 months, 929 for at least a year, and 750 for at least 2 years. More than 300 patients have been treated for 5 years or longer.

The most frequently reported adverse reactions were related to the gastrointestinal tract and included diarrhea, dyspepsia, and abdominal pain.

Incidence ≥1%—Probably Causally Related

Gastrointestinal: Diarrhea (14%), dyspepsia (13%), abdominal pain (12%), constipation*, flatulence*, nausea*, positive stool guaiac*, dry mouth, gastritis, stomatitis, vomiting.

Central Nervous System: Dizziness*, headache*, fatigue, increased sweating, insomnia, nervousness, somnolence.

Dermatologic: Pruritus*, rash*.

Special Senses: Tinnitus*.

Miscellaneous: Edema*.

*Incidence of reported reaction between 3% and 9%. Reactions occurring in 1% to 3% of the patients are unmarked.

Incidence <1%—Probably Causally Related†

Gastrointestinal: Anorexia, jaundice, duodenal ulcer, dysphagia, gastric ulcer, gastroenteritis, gastrointestinal bleeding, increased appetite, liver function abnormalities, melena, hepatic failure.

Central Nervous System: Asthenia, agitation, anxiety, confusion, depression, malaise, paresthesia, tremor, vertigo.

Dermatologic: Bullous eruptions, photosensitivity, urticaria, pseudoporphyria cutanea tarda, toxic epidermal necrolysis, erythema multiforme, Stevens-Johnson syndrome.

Cardiovascular: Vasculitis.

Metabolic: Weight gain.

Respiratory: Dyspnea, eosinophilic pneumonia, hypersensitivity pneumonitis, idiopathic interstitial pneumonitis.

Genitourinary: Albuminuria, azotemia, hyperuricemia, interstitial nephritis, nephrotic syndrome, vaginal bleeding, renal failure.

Special Senses: Abnormal vision.

Hematologic/Lymphatic: Thrombocytopenia.

Hypersensitivity: Anaphylactoid reaction, anaphylaxis, angioneurotic edema.

†Adverse reactions reported only in worldwide postmarketing experience or in the literature, not seen in clinical trials, are considered rarer and are italicized.

Incidence <1%—Causal Relationship Unknown

Gastrointestinal: Bilirubinuria, duodenitis, eructation, gallstones, gingivitis, glossitis, pancreatitis, rectal bleeding.

Central Nervous System: Nightmares.

Dermatologic: Acne, alopecia.

Cardiovascular: Angina, arrhythmia, hypertension, myocardial infarction, palpitations, syncope, thrombophlebitis.

Respiratory: Asthma, cough.

Genitourinary: Dysuria, hematuria, impotence, renal stones.

Special Senses: Taste disorder.

Body as a Whole: Fever, chills.

Hematologic/Lymphatic: Anemia, leukopenia, granulocytopenia.

Metabolic/Nutritional: Hyperglycemia, hypokalemia, weight loss.

OVERDOSAGE

Symptoms following acute NSAIDs overdoses are usually limited to lethargy, drowsiness, nausea, vomiting, and epigastric pain, which are generally reversible with supportive care. Gastrointestinal bleeding can occur. Hypertension, acute renal failure, respiratory depression, and coma may occur, but are rare. Anaphylactoid reactions have been reported with therapeutic ingestion of NSAIDs, and may occur following an overdose.

Patients should be managed by symptomatic and supportive care following a NSAIDs overdose. There are no specific antidotes. Emesis and/or activated charcoal (60 to 100 grams in adults, 1 to 2 g/kg in children), and/or osmotic cathartic may be indicated in patients seen within 4 hours of ingestion with symptoms or following a large overdose (5 to 10 times the usual dose). Forced diuresis, alkalinization of urine, hemodialysis, or hemoperfusion may not be useful due to high protein binding.

There have been overdoses of up to 25 grams of nabumetone reported with no long-term sequelae following standard emergency treatment (i.e., activated charcoal, gastric lavage, IV H2-blockers, etc.).

DOSAGE AND ADMINISTRATION

Carefully consider the potential benefits and risks of nabumetone tablets and other treatment options before deciding to use nabumetone tablets. Use the lowest effective dose for the shortest duration consistent with individual patient treatment goals (see WARNINGS).

After observing the response to initial therapy with nabumetone tablets, the dose and frequency should be adjusted to suit an individual patient’s needs.

Osteoarthritis and Rheumatoid Arthritis: The recommended starting dose is 1,000 mg taken as a single dose with or without food. Some patients may obtain more symptomatic relief from 1,500 mg to 2,000 mg per day. Nabumetone can be given in either a single or twice-daily dose. Dosages greater than 2,000 mg per day have not been studied. The lowest effective dose should be used for chronic treatment (see WARNINGS, Renal Effects). Patients weighing under 50 kg may be less likely to require dosages beyond 1,000 mg; therefore, after observing the response to initial therapy, the dose should be adjusted to meet individual patients’ requirements.

HOW SUPPLIED

Nabumetone tablets USP, 750 mg are white colored, oval shaped, biconvex, film coated tablets, debossed with ‘SG’ on one side ‘466’ on other side.

NDC

60760-369-14 BOTTLES OF 14

60760-369-60 BOTTLES OF 60

60760-369-90 BOTTLES OF 90

Store at 20° to 25°C (68° to 77°F); excursions permitted to 15° to 30°C (59° to 86°F) [see USP Controlled Room Temperature] in well-closed container; dispense in light-resistant container.

Rx Only

Medication Guide

for Non-Steroidal Anti-Inflammatory Drugs (NSAIDs)

What is the most important information I should know about medicines called Nonsteroidal Antiinflammatory Drugs (NSAIDs)?

NSAIDs can cause serious side effects, including:

• Increased risk of a heart attack or stroke that can lead to death. This risk may happen early in treatment and may increase:

• with increasing doses of NSAIDs

• with longer use of NSAIDs

Do not take NSAIDs right before or after a heart surgery called a “coronary artery bypass graft (CABG)."

Avoid taking NSAIDs after a recent heart attack, unless your healthcare provider tells you to. You may have an increased risk of another heart attack if you take NSAIDs after a recent heart attack.

• Increased risk of bleeding, ulcers, and tears (perforation) of the esophagus (tube leading from the mouth to the stomach), stomach and intestines:

• anytime during use

• without warning symptoms

• that may cause death

The risk of getting an ulcer or bleeding increases with:

• past history of stomach ulcers, or stomach or intestinal bleeding with use of NSAIDs

• taking medicines called “corticosteroids”, “anticoagulants”, “SSRIs”, or “SNRIs”

• increasing doses of NSAIDs

• longer use of NSAIDs

• smoking

• drinking alcohol

• older age

• poor health

• advanced liver disease

• bleeding problems

NSAIDs should only be used:

• exactly as prescribed

• at the lowest dose possible for your treatment

• for the shortest time needed

What are NSAIDs?

NSAIDs are used to treat pain and redness, swelling, and heat (inflammation) from medical conditions such as different types of arthritis, menstrual cramps, and other types of short-term pain.

Who should not take NSAIDs?

Do not take NSAIDs:

• if you have had an asthma attack, hives, or other allergic reaction with aspirin or any other NSAIDs.

• right before or after heart bypass surgery.

Before taking NSAIDS, tell your healthcare provider about all of your medical conditions, including if you:

• have liver or kidney problems

• have high blood pressure

• have asthma

• are pregnant or plan to become pregnant. Talk to your healthcare provivder if you are considering taking NSAIDs during pregnancy. You should not take NSAIDs after 29 weeks of pregnancy.

• are breastfeeding or plan to breast feed.

Tell your healthcare provider about all of the medicines you take, including prescription or over-the-counter medicines, vitamins or herbal supplements. NSAIDs and some other medicines can interact with each other and cause serious side effects. Do not start taking any new medicine without talking to your healthcare provider first.

What are the possible side effects of NSAIDs?

NSAIDs can cause serious side effects, including:

See “What is the most important information I should know about medicines called Nonsteroidal Antiinflammatory Drugs (NSAIDs)?

• new or worse high blood pressure

• heart failure

• liver problems including liver failure

• kidney problems including kidney failure

• low red blood cells (anemia)

• life-threatening skin reactions

• life threatening allergic reactions

• Other side effects of NSAIDs include: stomach pain, constipation, diarrhea, gas, heartburn, nausea, vomiting, and dizziness.

Get emergency help right away if you get any of the following symptoms:

• shortness of breath or trouble breathing

• chest pain

• weakness in one part or side of your body

• slurred speech

• swelling of the face or throat

Stop taking your NSAID and call your healthcare provider right away if you get any of the following symptoms:

• nausea

• more tired or weaker than usual

• diarrhea

• itching

• your skin or eyes look yellow

• indigestion or stomach pain

• flu-like symptoms

• vomit blood

• there is blood in your bowel movement or it is black and sticky like tar

• unusual weight gain

• skin rash or blisters with fever

• swelling of the arms, legs, hands and feet

If you take too much of your NSAID, call your healthcare provider or get medical help right away.

These are not all the possible side effects of NSAIDs. For more information, ask your healthcare provider or pharmacist about NSAIDs.

Call your doctor for medical advice about side effects. You may report side effects to FDA at 1-800-FDA-1088.

Other information about NSAIDs

• Aspirin is an NSAID but it does not increase the chance of a heart attack. Aspirin can cause bleeding in the brain, stomach, and intestines. Aspirin can also cause ulcers in the stomach and intestines.

• Some NSAIDs are sold in lower doses without a prescription (over-the counter). Talk to your healthcare provider before using over-the-counter NSAIDs for more than 10 days.

General information about the safe and effective use of NSAIDs

Medicines are sometimes prescribed for purposes other than those listed in a Medication Guide. Do not use NSAIDs for a condition for which it was not prescribed. Do not give NSAIDs to other people, even if they have the same symptoms that you have. It may harm them.

If you would like more information about NSAIDs, talk with your healthcare provider. You can ask your pharmacist or healthcare provider for information about NSAIDs that is written for health professionals.

For more information, call 1-855-724-3436.

This Medication Guide has been approved by the U.S. Food and Drug Administration.

Rx Only

Manufactured by:
ScieGen Pharmaceuticals, Inc.
Hauppauge, NY 11788

Revised: 07/19